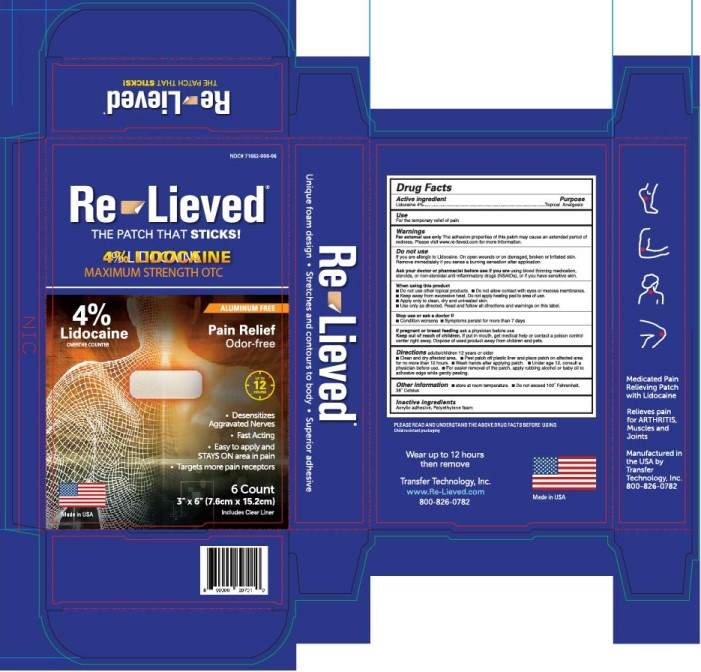 DRUG LABEL: Re-Lieved Lidocaine Patch
NDC: 71662-000 | Form: PATCH
Manufacturer: Transfer Technology
Category: otc | Type: HUMAN OTC DRUG LABEL
Date: 20250111

ACTIVE INGREDIENTS: LIDOCAINE 18 mg/116 cm2
INACTIVE INGREDIENTS: ACRYLIC ACID/ETHYLENE COPOLYMER (600 MPA.S)

Re-Lieved Lidocaine 4% Patch, Six Foam Patches per Box

Active Ingredients

Lidocaine 4%

Purpose

Topical Analgesic

Indications & Usage

For the temporary relief of pain.

Warnings

For external use only.The adhesoin properties of this patch may cause an extended period of redness. Please visit www.re-lieved.com for more information.

Do not use

If you are allergic to Lidocaine. On open wounds or on damaged, broken or irritated skin. Remove immidiately if you sense a burning sensation after application.

When using this product

- Do not use other topical products
- Do not allow contact with eyes or mucous membranes
- Keep away from excessive heat. Do not apply heating pad to area of use
- Apply only to clean, dry and untreated skin
- Use only as directed. Read and follow all directions and warnings on this label

Ask your doctor or pharmacist before use if you are

using blood thinning medication, steroids, or non-steroidal anti-inflammatory druns (NSAIDs), or if you have sensitive skin.

Stop use or ask a doctor if

- Condition worsens
- Symptoms persist for more than 7 days

If pregnant or breast feeding

ask a physician before use.

Keep out of reach of children

If put in mouth, get medical help or contact a poison control center right away. Dispose of used product away from children and pets.

Directions:

- Clean and dry affected area
- Peel patch off plastic liner and place on affected area for no more than 12 hours
- Wash hands after applying patch.
- Under age 12, consult a physician before use
- For easier removal of the patc, apply rubbing alcohol or baby oil to adhesive edge while gently peeling

Other information

- store at room termperature
- Do not exceed 100oFahrenheit, 38oCelsius

Inactive Ingredients

Acrylic adhesive, Polyethylene fabric